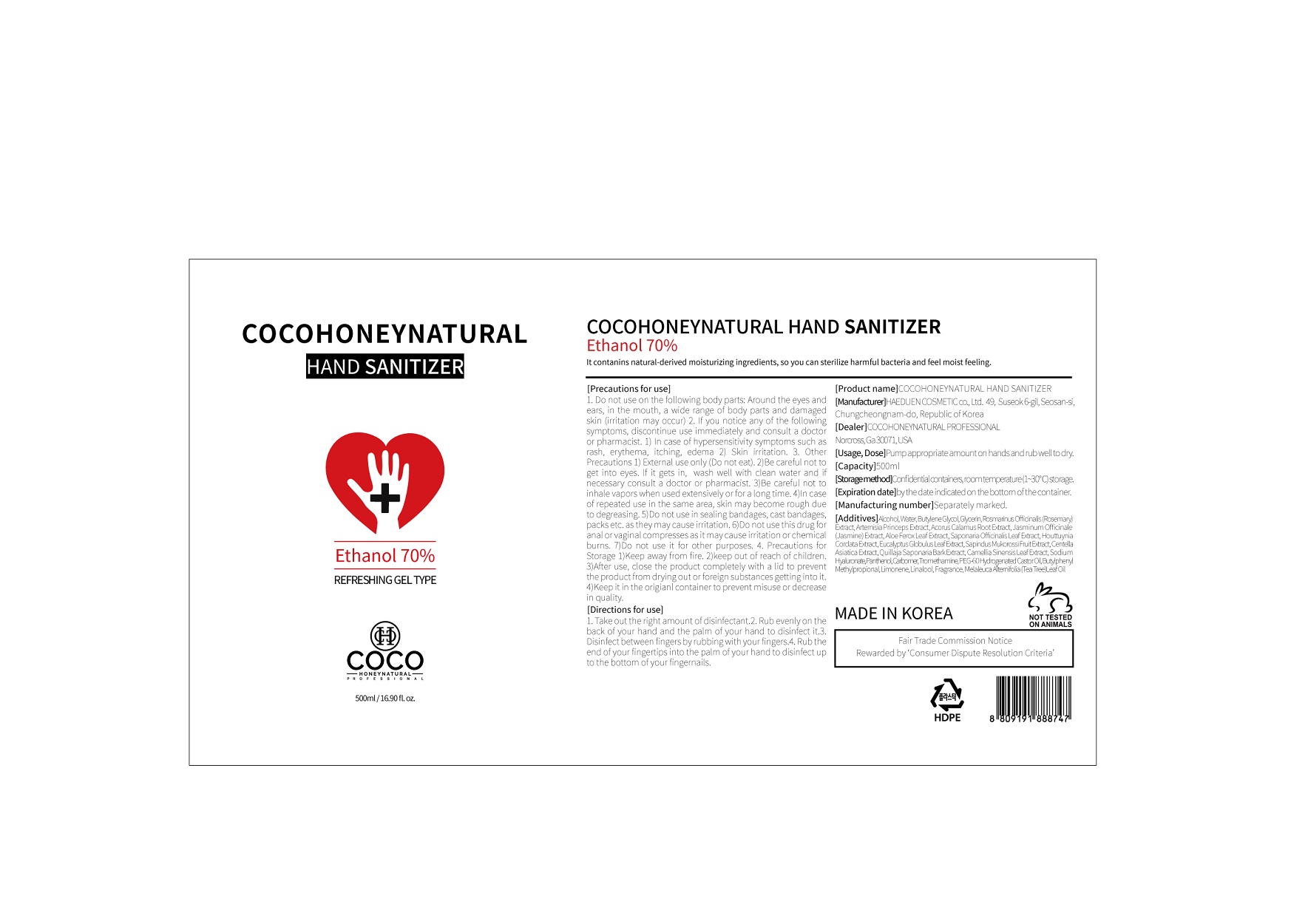 DRUG LABEL: COCOHONEYNATURAL HAND SANITIZER
NDC: 76674-0001 | Form: LIQUID
Manufacturer: Haeduen Cosmetics
Category: otc | Type: HUMAN OTC DRUG LABEL
Date: 20200501

ACTIVE INGREDIENTS: ALCOHOL 70 mL/100 mL
INACTIVE INGREDIENTS: TROLAMINE; WATER; ALOE VERA LEAF; CARBOMER 940; BUTYLENE GLYCOL

Drug Facts

ACTIVE INGREDIENT

alcohol

PURPOSE

sterilization of hands, skin and so on

KEEP OUT OF REACH OF THE CHILDREN

INDICATIONS AND USAGE

use appropriate amount on the hand, rub and dry well

WARNINGS

■ Flammable. Keep away from fire or flame.

■ For external use only.

■ Do not use in eyes.

■ lf swallowed, get medical help promptly.

■ Stop use, ask doctor lf irritation occurs.

■ Keep out of reach of children.

DOSAGE AND ADMINISTRATION

for external use only

INACTIVE INGREDIENT

water, butylene glycol, glycerin, rosemary extract, etc (see attached label)